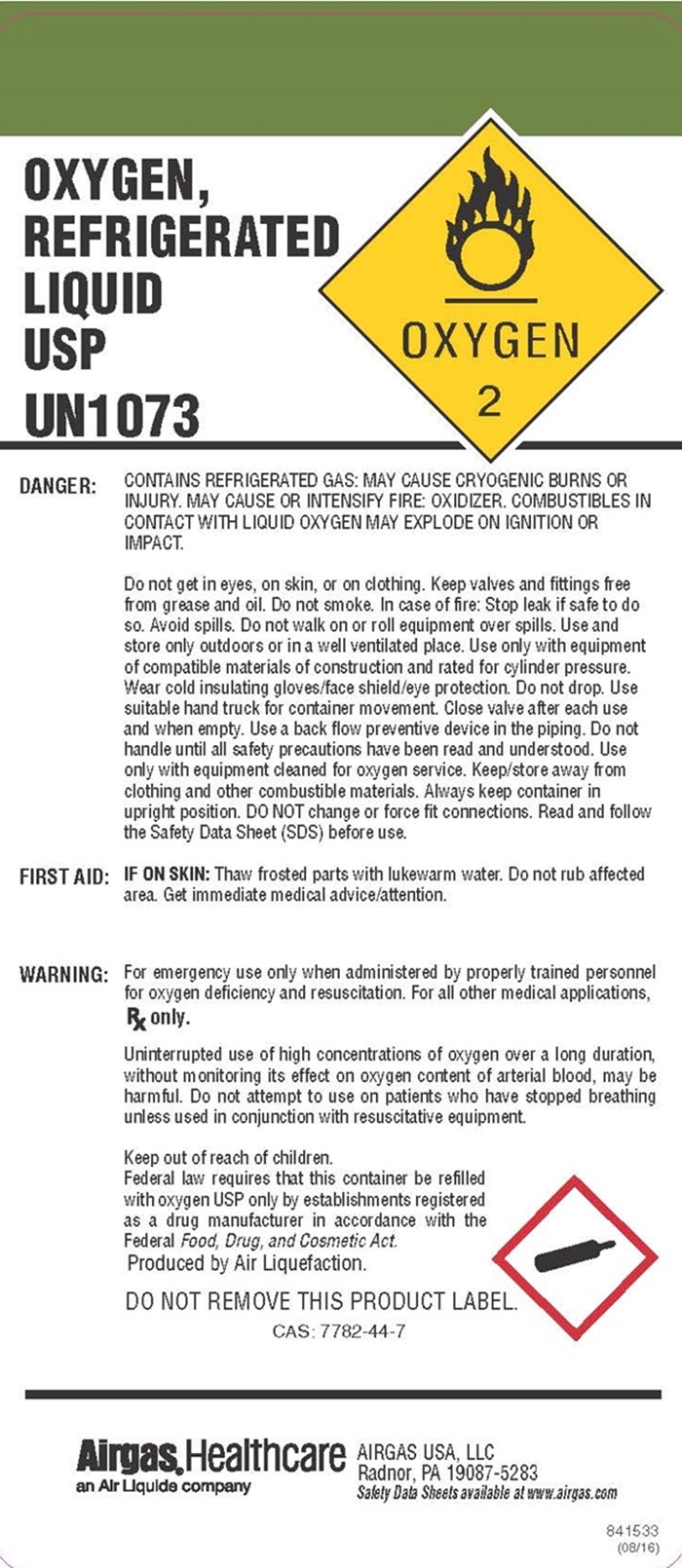 DRUG LABEL: Oxygen, Refrigerated
NDC: 11054-010 | Form: GAS
Manufacturer: AIRGAS USA, LLC
Category: prescription | Type: HUMAN PRESCRIPTION DRUG LABEL
Date: 20260212

ACTIVE INGREDIENTS: Oxygen 992 mL/1 L

Oxygen, Refrigerated Liquid - 010

Oxygen Refrigerated product label

OXYGEN,
REFRIGERATED
LIQUID
USP

UN1073

OXYGEN 2

DANGER: CONTAINS REFRIGERATED GAS: MAY CAUSE CRYOGENIC BURNS OR INJURY. MAY CAUSE OR INTENSIFY FIRE: OXIDIZER. COMBUSTIBLES IN CONTACT WITH LIQUID OXYGEN MAY EXPLODE ON IGNITION OR IMPACT.

Do not get into eyes, on skin, or on clothing. Keep valves and fittings free from grease and oil. Do not smoke. In case of fire: Stop leak if safe to do so. Avoid spills. Do not walk or roll equipment over spills. Use and store only outdoors or in a well ventilated place. Use only with equipment of compatible materials of construction and rated for cylinder pressure. Wear cold insulating gloves/face shield/eye protection. Do not drop. Use suitable hand truck for container movement. Close valve after each use and when empty. Use a back flow preventive device in the piping. Do not handle until all safety precautions have been read and understood. Use only with equipment cleaned for oxygen service. Keep/store away from clothing and other combustible materials. Always keep container in upright position. DO NOT change or force fit connections. Read and follow the Safety Data Sheet (SDS) before use.

FIRST AID: IF ON SKIN: Thaw frosted parts with lukewarm water. Do not rub affected area. Get immediate medical attention.

WARNING: For emergency use only when administered by properly trained personnel for oxygen deficienct and resuscitation. For all other medical applications Rx only.

Uninterrupted use of high concentrations of oxygen over a long duration, without monitoring its effect on oxygen content of arterial blood, may be harmful. Do not attempt to use on patients who have stoped breating unless used in conjunction with resuscitative equipment.

Keep out of reach of children.

Federal law required that this container be refilled with Oxyhen USP only by establishments registered as a drug manufacture in accordance with the Federal Food, Drug, and Cosmetic Act.

DO NOT REMOVE THIS PRODUCT LABEL

CAS: 7782-44-7

AIRGAS® Healthcare
an Air Liquide Company
AIRGAS USA, LLC
Radnor, PA 19087-5283

Safety Data Sheets available at www.airgas.com

84 1533
(08/16)